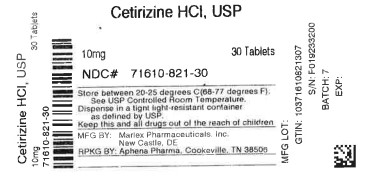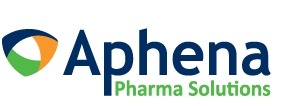 DRUG LABEL: Cetirizine Hydrochloride
NDC: 71610-821 | Form: TABLET
Manufacturer: Aphena Pharma Solutions - Tennessee, LLC		
Category: otc | Type: HUMAN OTC DRUG LABEL
Date: 20240412

ACTIVE INGREDIENTS: CETIRIZINE HYDROCHLORIDE 10 mg/1 1
INACTIVE INGREDIENTS: POVIDONE, UNSPECIFIED; LACTOSE MONOHYDRATE; MAGNESIUM STEARATE; STARCH, CORN; TALC; TITANIUM DIOXIDE; HYPROMELLOSE, UNSPECIFIED; POLYETHYLENE GLYCOL, UNSPECIFIED

Cetirizine Hydrochloride

Drug Facts

Active ingredient (in each tablet)

Cetirizine HCl, USP 10 mg

Purpose

Antihistamine

Uses

temporarily relieves these symptoms due to hay fever or other upper respiratory allergies:

- runny nose
- sneezing
- itchy, watery eyes
- itching of the nose or throat

Warnings

DO NOT USE

Do not useif you have ever had an allergic reaction to this product or any of its ingredients or to an antihistamine containing hydroxyzine.

Ask a doctor before use if you haveliver or kidney disease. Your doctor should determine if you need a different dose.

Ask a doctor or pharmacist before use if you aretaking tranquilizers or sedatives.

When using this product

- drowsiness may occur
- avoid alcoholic drinks
- alcohol, sedatives, and tranquilizers may increase drowsiness
- be careful when driving a motor vehicle or operating machinery

Stop use and ask a doctor ifan allergic reaction to this product occurs. Seek medical help right away.

If pregnant or breast-feeding

- if breast-feeding: not recommended
- if pregnant: ask a health professional before use.

Keep out of reach of children.In case of overdose, get medical help or contact a Poison Control Center right away (1-800-222-1222).

Directions

adults and children 6 years and over | one 10 mg tablet once daily; do not take more than one 10 mg tablet in 24 hours. A 5 mg product may be appropriate for less severe symptoms.
adults 65 years and over | ask a doctor
children under 6 years of age | ask a doctor
consumers with liver or kidney disease | ask a doctor

Other information

- TAMPER EVIDENT: DO NOT USE IF IMPRINTED SEAL IS BROKEN OR MISSING FROM BOTTLE.
- store between 20° to 25° C (68° to 77° F)

Inactive ingredients

corn starch, hypromellose, lactose monohydrate, magnesium stearate, polyethylene glycol, povidone, talc, titanium dioxide

Manufactured for/ Distributed by:

Marlex Pharmaceuticals, Inc.

New Castle, DE 19720

Rev. 10/22 SP

REPACKAGING INFORMATION

Please reference the HOW SUPPLIED section listed above for a description of individual drug products listed below. This drug product has been received by Aphena Pharma Solutions - Tennessee, LLC in a manufacturer or distributor packaged configuration and repackaged in full compliance with all applicable cGMP regulations. The package configurations available from Aphena are listed below:

10mg
NDC 71610-821-30, Bottles of 30 Tablets
NDC 71610-821-60, Bottles of 90 Tablets

Store between 20°-25°C (68°-77°F). See USP Controlled Room Temperature. Dispense in a tight light-resistant container as defined by USP. Keep this and all drugs out of the reach of children.
Repackaged by:

Cookeville, TN 38506

20240412AMH

PRINCIPAL DISPLAY PANEL - 10mg

NDC 71610-821 - Cetirizine HCl, USP 10mg Tablets - Rx Only